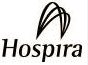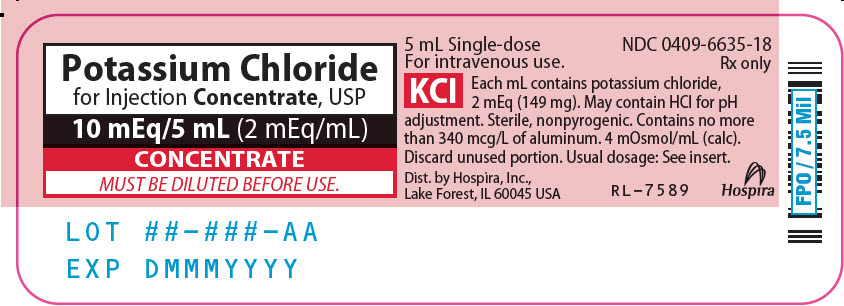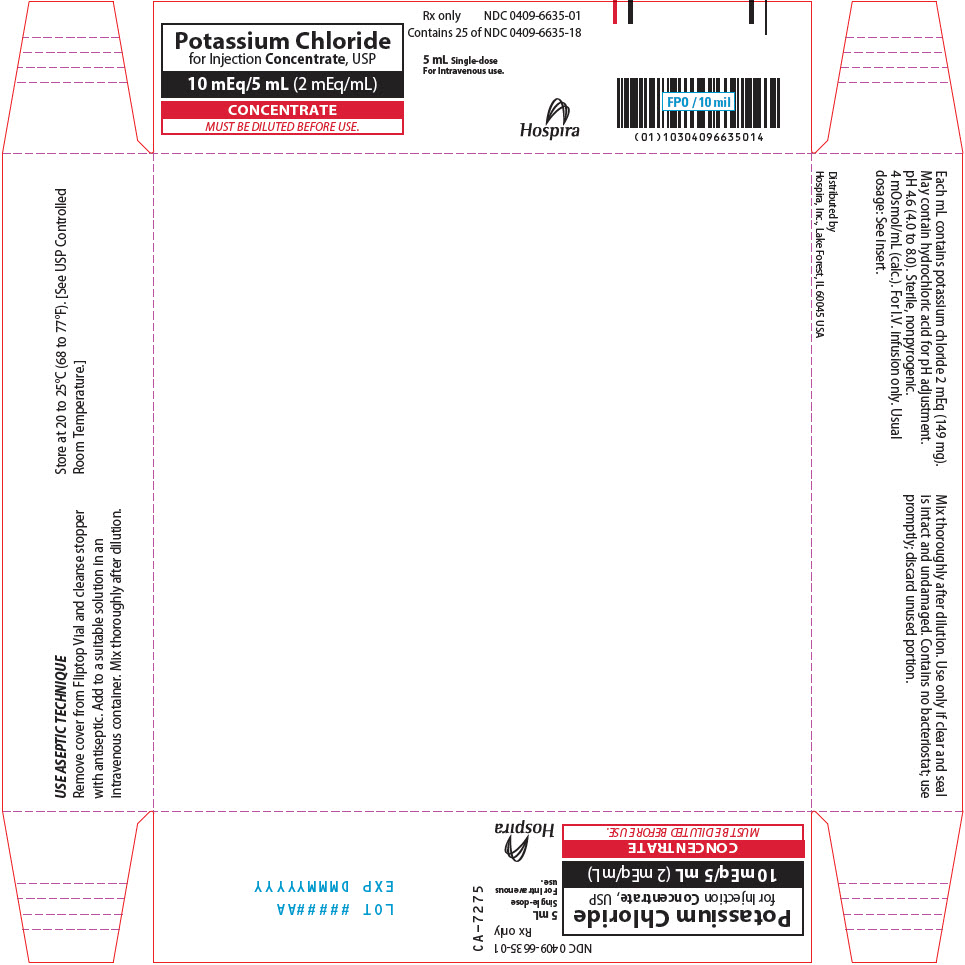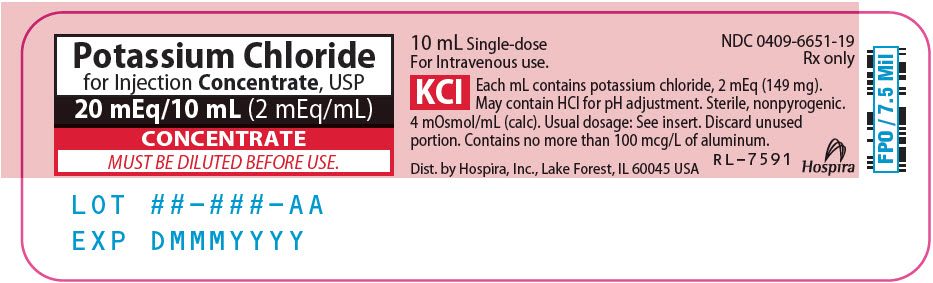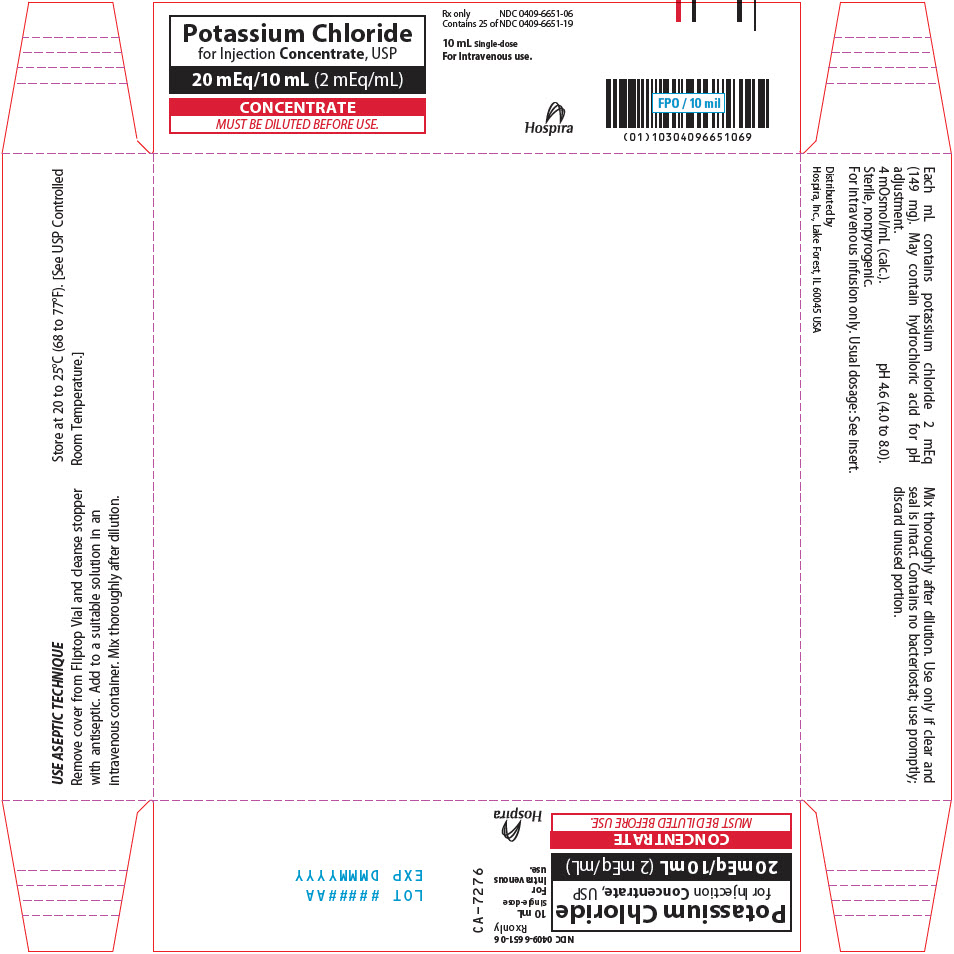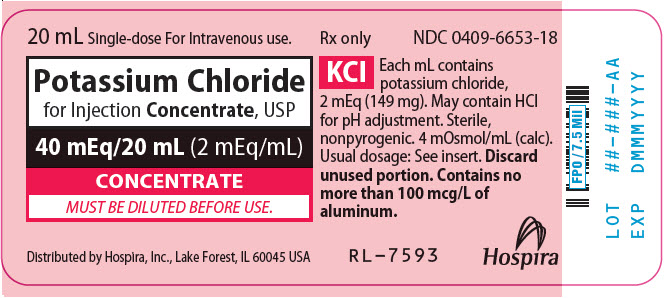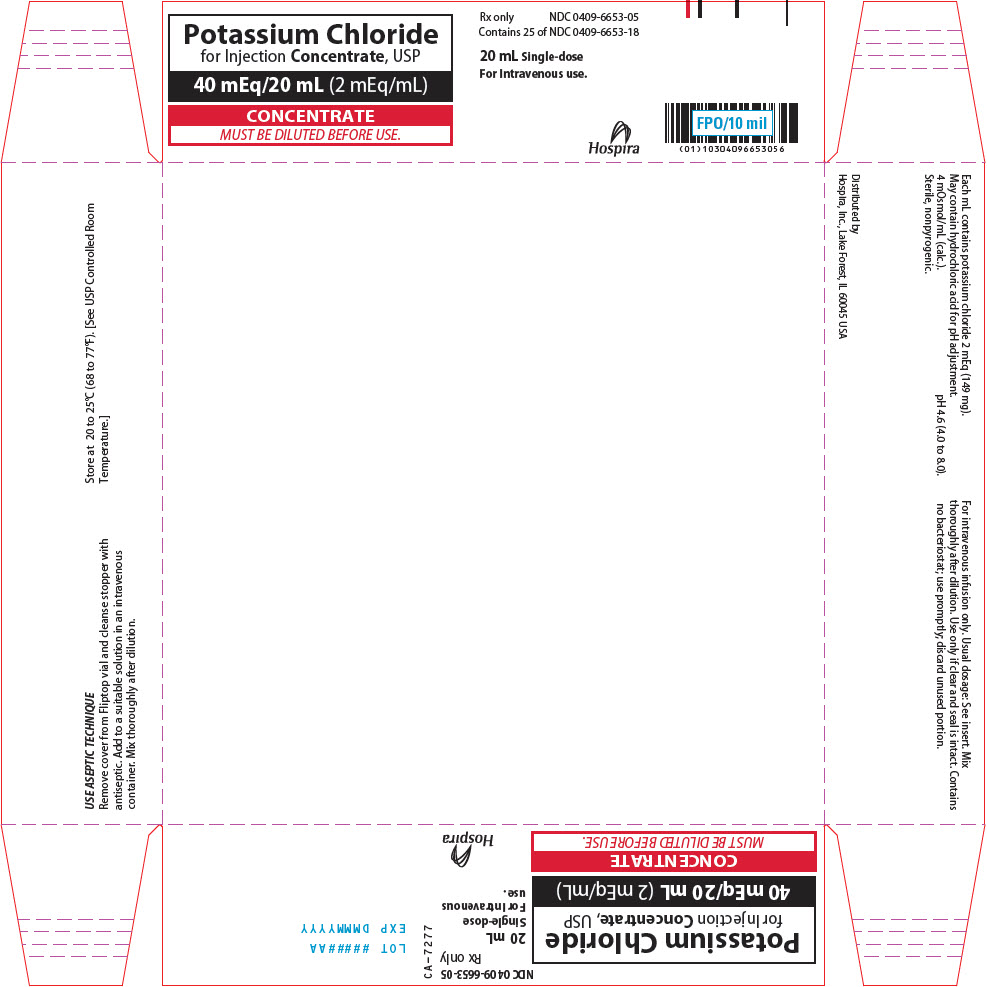 DRUG LABEL: POTASSIUM CHLORIDE
NDC: 0409-6635 | Form: INJECTION, SOLUTION, CONCENTRATE
Manufacturer: Hospira, Inc.
Category: prescription | Type: HUMAN PRESCRIPTION DRUG LABEL
Date: 20260203

ACTIVE INGREDIENTS: POTASSIUM CHLORIDE 149 mg/1 mL
INACTIVE INGREDIENTS: WATER; HYDROCHLORIC ACID

Potassium Chloride Rx only

for Injection
Concentrate, USP

CONCENTRATE

MUST BE DILUTED BEFORE USE.

FOR INTRAVENOUS INFUSION ONLY;
MUST BE DILUTED PRIOR TO INJECTION.
Fliptop Vials

DESCRIPTION

Potassium Chloride for Injection Concentrate, USP, is a sterile, nonpyrogenic, concentrated solution of potassium chloride, USP in water for injection administered by intravenous infusion only after dilution in a larger volume of fluid. They are provided in the following variety of concentrations and sizes comprising a choice of single-dose containers, all designed to provide the commonly prescribed amounts of potassium chloride for single-dose infusion after dilution in suitable large volume parenterals.

Additive Solution [May contain hydrochloric acid for pH adjustment.]; (conc. & size) | K^+; mEq/mL | KCl; mg/mL | mOsmol/mL; (calc.)
10 mEq/5 mL | 2 | 149 | 4
20 mEq/10 mL | 2 | 149 | 4
40 mEq/20 mL | 2 | 149 | 4

The solutions contain no bacteriostat, antimicrobial agent or added buffer (except for pH adjustment) and each is intended only for single-dose injection (after dilution). When smaller doses are required, discard the unused portion. The pH is 4.6 (4.0 to 8.0).

Potassium Chloride for Injection Concentrate, USP (appropriately diluted) is a parenteral fluid and electrolyte replenisher.

Potassium Chloride, USP is chemically designated KCl, a white granular powder freely soluble in water.

The semi-rigid material used for the plastic vials is fabricated from a specially formulated polyolefin. It is a copolymer of ethylene and propylene. The safety of the plastic has been confirmed by tests in animals according to USP biological standards for plastic containers. The container requires no vapor barrier to maintain the proper drug concentration.

CLINICAL PHARMACOLOGY

Potassium is the chief cation of body cells (160 mEq/liter of intracellular water) and is concerned with the maintenance of body fluid composition and electrolyte balance. Potassium participates in carbohydrate utilization and protein synthesis, and is critical in the regulation of nerve conduction and muscle contraction, particularly in the heart. Chloride, the major extracellular anion, closely follows the metabolism of sodium, and changes in the acid-base balance of the body are reflected by changes in the chloride concentration.

Normally about 80 to 90% of the potassium intake is excreted in the urine, the remainder in the stools and, to a small extent, in perspiration. The kidney does not conserve potassium well so that during fasting, or in patients on a potassium-free diet, potassium loss from the body continues, resulting in potassium depletion. A deficiency of either potassium or chloride will lead to a deficit of the other.

INDICATIONS AND USAGE

Potassium Chloride for Injection Concentrate, USP is indicated in the treatment of potassium deficiency states when oral replacement is not feasible.

CONTRAINDICATIONS

Potassium Chloride for Injection Concentrate, USP is contraindicated in diseases where high potassium levels may be encountered, and in patients with hyperkalemia, renal failure and in conditions in which potassium retention is present.

WARNINGS

Potentially Fatal Cardiac Adverse Reactions with Undiluted Intravenous Administration

Direct patient injection of potassium chloride at this concentration may be instantaneously fatal. Potassium Chloride for Injection Concentrate must be diluted before administration. Fatal cardiac arrhythmia and cardiac arrest have occurred when potassium chloride was administered in an undiluted form.

To avoid potassium intoxication, do not infuse these solutions rapidly. In patients with renal insufficiency, administration of potassium chloride may cause potassium intoxication and life-threatening hyperkalemia.

The administration of intravenous solutions can cause fluid and/or solute overload resulting in dilution of serum electrolyte concentrations, overhydration, congested states or pulmonary edema. The risk of dilutional states is inversely proportional to the electrolyte concentration. The risk of solute overload causing congested states with peripheral and pulmonary edema is directly proportional to the electrolyte concentration.

In patients with diminished renal function, administration of solutions containing potassium ions may result in potassium retention.

This product contains aluminum that may be toxic. Aluminum may reach toxic levels with prolonged parenteral administration if kidney function is impaired. Premature neonates are particularly at risk because their kidneys are immature, and they require large amounts of calcium and phosphate solutions, which contain aluminum.

Research indicates that patients with impaired kidney function, including premature neonates, who receive parenteral levels of aluminum at greater than 4 to 5 mcg/kg/day accumulate aluminum at levels associated with central nervous system and bone toxicity. Tissue loading may occur at even lower rates of administration.

PRECAUTIONS

General

Clinical evaluation and periodic laboratory determinations are necessary to monitor changes in fluid balance, electrolyte concentrations, and acid-base balance during prolonged parenteral therapy or whenever the condition of the patient warrants such evaluation. Significant deviations from normal concentrations may require the use of additional electrolyte supplements, or the use of electrolyte-free dextrose solutions to which individualized electrolyte supplements may be added.

Potassium therapy should be guided primarily by serial electrocardiograms, especially in patients receiving digitalis. Serum potassium levels are not necessarily indicative of tissue potassium levels. Solutions containing potassium should be used with caution in the presence of cardiac disease, particularly in the presence of renal disease, and in such instances, cardiac monitoring is recommended.

Solutions containing dextrose should be used with caution in patients with overt or known subclinical diabetes mellitus, or carbohydrate intolerance for any reason.

If the administration is controlled by a pumping device, care must be taken to discontinue pumping action before the container runs dry or air embolism may result.

Pregnancy

Teratogenic Effects: Animal reproduction studies have not been conducted with potassium chloride. It is also not known whether potassium chloride can cause fetal harm when administered to a pregnant woman or can affect reproduction capacity. Potassium chloride should be given to a pregnant woman only if clearly needed.

ADVERSE REACTIONS

Reactions which may occur because of the solution or the technique of administration include febrile response, infection at the site of injection, venous thrombosis or phlebitis extending from the site of injection, extravasation, hypervolemia, and hyperkalemia.

Too rapid infusion of hypertonic solutions may cause local pain and, rarely, vein irritation. Rate of administration should be adjusted according to tolerance.

Reactions reported with the use of potassium-containing solutions include nausea, vomiting, abdominal pain and diarrhea. The signs and symptoms of potassium intoxication include paresthesias of the extremities, areflexia, muscular or respiratory paralysis, mental confusion, weakness, hypotension, cardiac arrhythmias, heart block, electrocardiographic abnormalities and cardiac arrest. Potassium deficits result in disruption of neuromuscular function, and intestinal ileus and dilatation.

If an adverse reaction does occur, discontinue the infusion, evaluate the patient, institute appropriate therapeutic countermeasures and save the remainder of the fluid for examination if deemed necessary.

OVERDOSAGE

In the event of fluid overload during parenteral therapy, re-evaluate the patient's condition, and institute appropriate corrective treatment.

In the event of overdosage with potassium-containing solutions, discontinue the infusion immediately, and institute corrective therapy to reduce serum potassium levels.

Treatment of hyperkalemia includes the following:

1. Dextrose Injection USP, 10% or 25%, containing 10 units of crystalline insulin per 20 grams of dextrose administered intravenously, at a rate of 300 to 500 mL per hour.
2. Absorption and exchange of potassium using sodium or ammonium cycle cation exchange resin, orally and as retention enema.
3. Hemodialysis and peritoneal dialysis. The use of potassium-containing foods or medications must be eliminated. However, in cases of digitalization, too rapid a lowering of plasma potassium concentration can cause digitalis toxicity.

DOSAGE AND ADMINISTRATION

Potassium Chloride for Injection Concentrate, USP must be diluted before administration. Care must be taken to ensure there is complete mixing of the potassium chloride with the large volume fluid, particularly if soft or bag type containers are used.

The dose and rate of administration are dependent upon the specific condition of each patient.

If the serum potassium level is greater than 2.5 mEq/liter, potassium can be given at a rate not to exceed 10 mEq/hour in a concentration of up to 40 mEq/liter. The 24-hour total dose should not exceed 200 mEq.

If urgent treatment is indicated (serum potassium level less than 2.0 mEq/liter with electrocardiographic changes and/or muscle paralysis) potassium chloride may be infused very cautiously at a rate of up to 40 mEq/hour. In such cases, continuous cardiac monitoring is essential. As much as 400 mEq may be administered in a 24 hour period. In critical conditions, potassium chloride may be administered in saline (unless contraindicated), rather than in dextrose containing fluids, as dextrose may lower serum potassium levels.

Prior to entering vial, remove the metal seal and cleanse the rubber closure with a suitable antiseptic agent.

Parenteral drug products should be inspected visually for particulate matter and discoloration, whenever solution and container permit.

TO PREVENT NEEDLE-STICK INJURIES, NEEDLES SHOULD NOT BE RECAPPED, PURPOSELY BENT, OR BROKEN BY HAND.

HOW SUPPLIED

Potassium Chloride for Injection Concentrate, USP, is supplied in single-dose containers as follows:

Unit of Sale | Concentration
NDC 0409-6635-01 Tray of 25 single-dose containers | 10 mEq/5 mL (2 mEq/mL)
NDC 0409-6651-06 Tray of 25 single-dose containers | 20 mEq/10 mL (2 mEq/mL)
NDC 0409-6653-05 Tray of 25 single-dose containers | 40 mEq/20 mL (2 mEq/mL)

Store at 20 to 25°C (68 to 77°F). [See USP Controlled Room Temperature.]

Distributed by: Hospira Inc., Lake Forest, IL 60045 USA

LAB-1319-3.0

Revised: 01/2026

PRINCIPAL DISPLAY PANEL - 5 mL Vial Label

Potassium Chloride
for Injection Concentrate, USP

10 mEq/5 mL (2 mEq/mL)

CONCENTRATE
MUST BE DILUTED BEFORE USE.

LOT ##–###–AA
EXP DMMMYYYY

PRINCIPAL DISPLAY PANEL - 5 mL Vial Tray

Potassium Chloride
for Injection Concentrate, USP

10 mEq/5 mL (2 mEq/mL)

CONCENTRATE
MUST BE DILUTED BEFORE USE.

Rx only
NDC 0409-6635-01
Contains 25 of NDC 0409-6635-18

5 mL Single-dose
For Intravenous use.

Hospira

PRINCIPAL DISPLAY PANEL - 10 mL Vial Label

Potassium Chloride
for Injection Concentrate, USP

20 mEq/10 mL (2 mEq/mL)

CONCENTRATE
MUST BE DILUTED BEFORE USE.

LOT ##–###–AA
EXP DMMMYYYY

PRINCIPAL DISPLAY PANEL - 10 mL Vial Tray

Potassium Chloride
for Injection Concentrate, USP

20 mEq/10 mL (2 mEq/mL)

CONCENTRATE
MUST BE DILUTED BEFORE USE.

Rx only
NDC 0409-6651-06
Contains 25 of NDC 0409-6651-19

10 mL Single-dose
For Intravenous use.

Hospira

PRINCIPAL DISPLAY PANEL - 20 mL Vial Label

20 mL Single-dose For Intravenous use.

Potassium Chloride
for Injection Concentrate, USP

40 mEq/20 mL (2 mEq/mL)

CONCENTRATE
MUST BE DILUTED BEFORE USE.

Distributed by Hospira, Inc., Lake Forest, IL 60045 USA

PRINCIPAL DISPLAY PANEL - 20 mL Vial Tray

Potassium Chloride
for Injection Concentrate, USP

40 mEq/20 mL (2 mEq/mL)

CONCENTRATE
MUST BE DILUTED BEFORE USE.

Rx only
NDC 0409-6653-05
Contains 25 of NDC 0409-6653-18

20 mL Single-dose
For Intravenous use.

Hospira